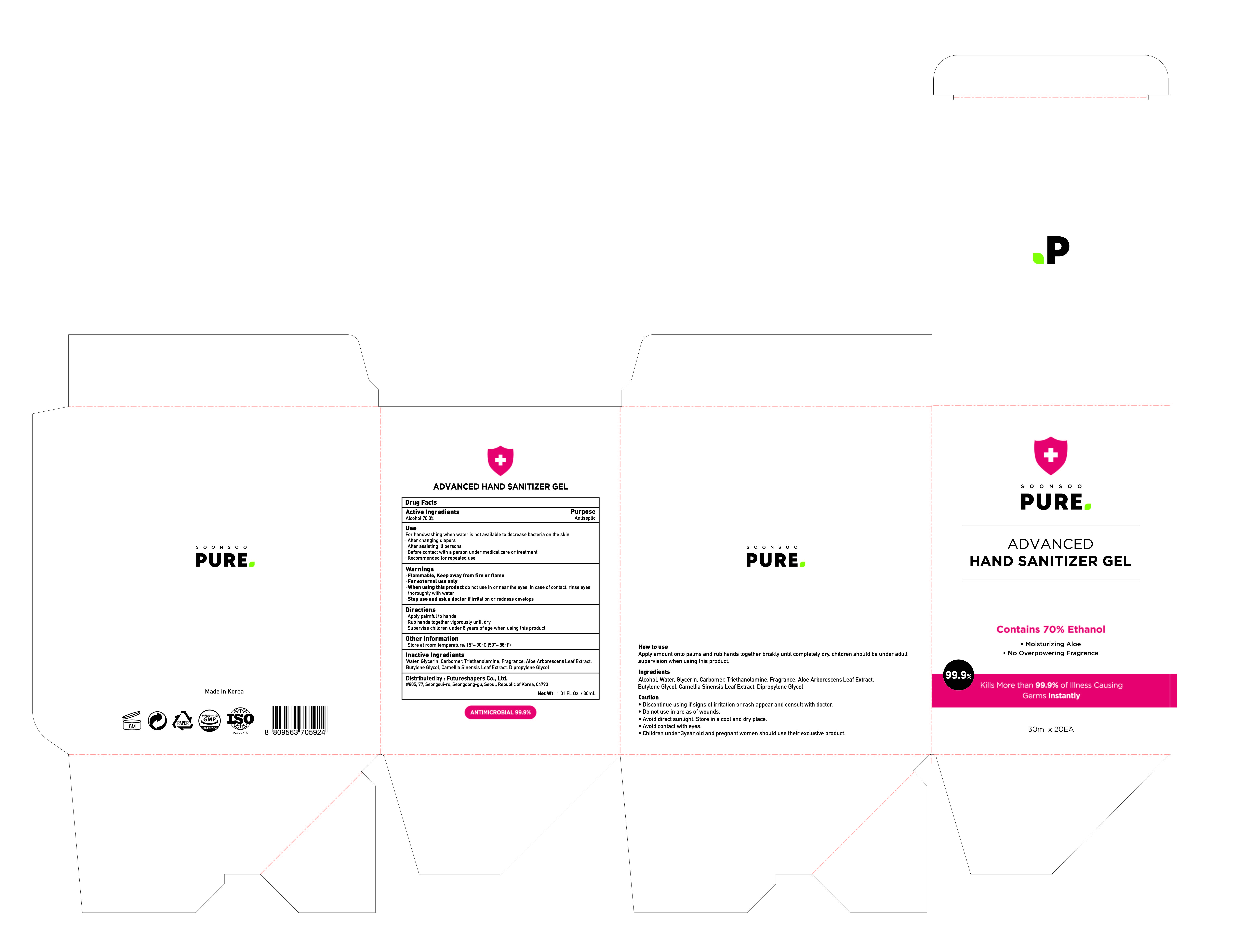 DRUG LABEL: Soonsoo Pure Advanced Hand Sanitizer Gel
NDC: 74004-371 | Form: GEL
Manufacturer: Ester Co., Ltd.
Category: otc | Type: HUMAN OTC DRUG LABEL
Date: 20200624

ACTIVE INGREDIENTS: ALCOHOL 21 mL/30 mL
INACTIVE INGREDIENTS: DIPROPYLENE GLYCOL; BUTYLENE GLYCOL; GREEN TEA LEAF; CARBOMER HOMOPOLYMER, UNSPECIFIED TYPE; WATER; TROLAMINE; GLYCERIN; ALOE VERA LEAF

[Ester Co., Ltd.-Soonsoo Pure Advanced Hand Sanitizer Gel] 30 ml in 1 pouch < 20 pouch in 1 box : 74004-371-20
Red